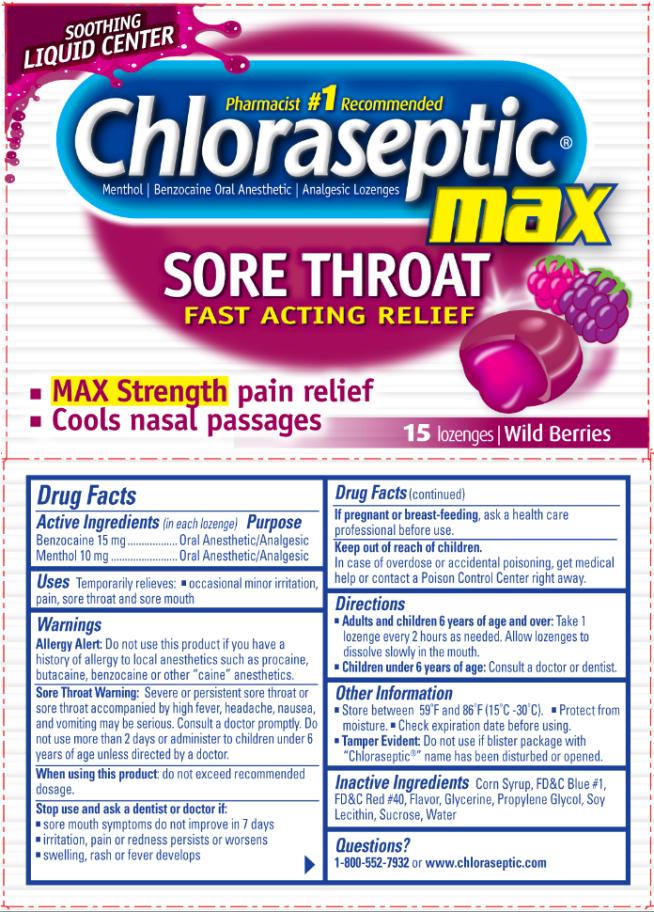 DRUG LABEL: Chloraseptic Sore Throat Max Liquid Center
NDC: 67172-174 | Form: LOZENGE
Manufacturer: Prestige Brands Holdings, Inc.
Category: otc | Type: HUMAN OTC DRUG LABEL
Date: 20101119

ACTIVE INGREDIENTS: MENTHOL 10 mg/1 1; BENZOCAINE 15 mg/1 1
INACTIVE INGREDIENTS: CORN SYRUP; FD&C BLUE NO. 1; FD&C RED NO. 40; GLYCERIN; LECITHIN, SOYBEAN; SUCROSE; WATER; PROPYLENE GLYCOL

Chloraseptic Max Berry Lozenges

Drug Facts

Active Ingredients

(in each lozenge)

Benzocaine 15 mg

Purpose

Oral Anesthetic/Analgesic

Active Ingredients

(in each lozenge)

Menthol 10 mg

Purpose

Oral Anesthetic/Analgesic

Uses

Temporarily relieves:

- occasional minor irritation, pain, sore throat and sore mouth

Warnings

Allergy Alert: Do not use this product if you have a history of allergy to local anesthetics such as procaine, butacaine, benzocaine or other “caine” anesthetics.

Sore Throat Warning: Severe or persistent sore throat or sore throat accompanied by high fever, headache, nausea and vomiting may be serious. Consult a doctor promptly. Do not use more than 2 days or administer to children under 6 years of age unless directed by a doctor.

When using this product:

do not exceed recommended dosage.

Stop use and ask a dentist or doctor if:

- sore mouth symptoms do not improve in 7 days
- irritation, pain or redness persists or worsens
- swelling, rash or fever develops

If pregnant or breast-feeding,

ask a health care professional before use.

Keep out of reach of children.

In case of overdose or accidental poisoning, get medical help or contact a Poison Control Center right away.

Directions

- Adults and children 6 years of age and over: Take 1 lozenge every 2 hours as needed. Allow lozenges to dissolve slowly in the mouth.
- Children under 6 years of age: Consult a doctor or dentist.

Other Information

- Store between 59ºF and 86ºF (15ºC - 30ºC).
- Protect from moisture.
- Check expiration date before using.
- Tamper Evident: Do not use if blister package with “Chloraseptic®” name has been disturbed or opened.

Inactive Ingredients

Corn Syrup, FD&C Blue #1, FD&C Red #40, Flavor, Glycerine, Propylene Glycol, Soy Lecithin, Sucrose, Water

Questions?

1-800-552-7932 or www.chloraseptic.com

PRINCIPAL DISPLAY PANEL

Chloraseptic® Max
SORE THROAT FAST ACTING RELIEF
15 lozenges | Wild Berries